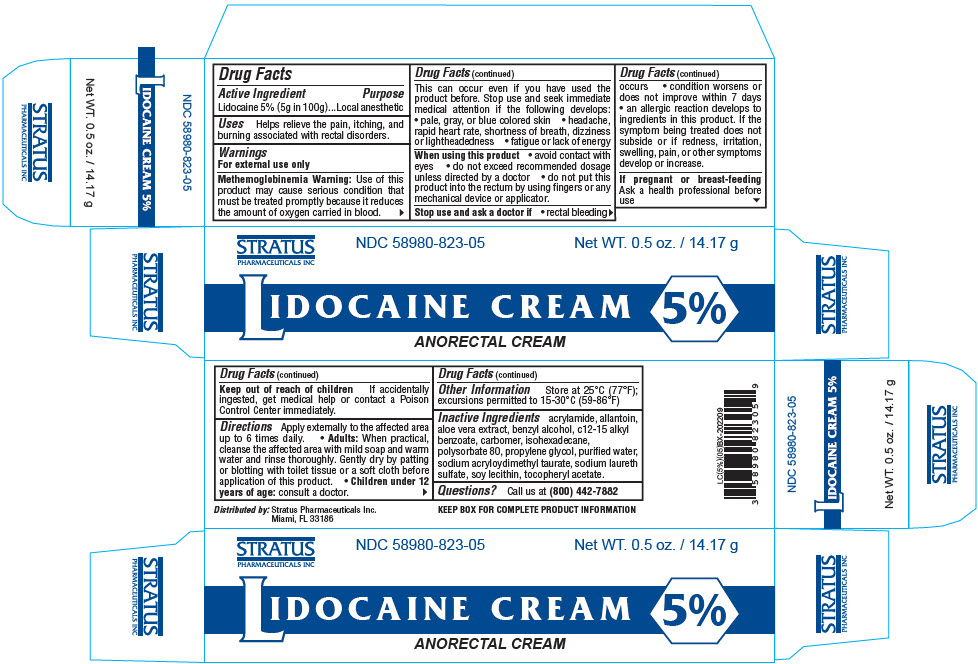 DRUG LABEL: LIDOCAINE
NDC: 58980-823 | Form: CREAM
Manufacturer: STRATUS PHARMACEUTICALS INC
Category: otc | Type: HUMAN OTC DRUG LABEL
Date: 20241101

ACTIVE INGREDIENTS: LIDOCAINE 50 mg/1 g
INACTIVE INGREDIENTS: ACRYLAMIDE; ALLANTOIN; ALOE VERA LEAF; BENZYL ALCOHOL; ALKYL (C12-15) BENZOATE; CARBOMER HOMOPOLYMER, UNSPECIFIED TYPE; ISOHEXADECANE; POLYSORBATE 80; PROPYLENE GLYCOL; WATER; SODIUM ACRYLOYLDIMETHYLTAURATE; SODIUM LAURETH-3 SULFATE; SOYBEAN LECITHIN; .ALPHA.-TOCOPHEROL ACETATE

LIDOCAINE 5% CREAM

Drug Facts

Active Ingredient

Lidocaine 5% w/w

Purpose

Local anesthetic

Uses

Helps relieve the pain, itching, and burning associated with other rectal disorders.

WARNINGS

"Methemoglobinemia Warning" use of this product may cause; a serious condition that must be treated promptly because it reduces the amount of oxygen carried in blood. This can occur even if you have used the product before. Stop use and seek immediate medical attention if the following develops: pale, gray, or blue colored skin (cyanosis), headache, rapid heart rate, shortness of breath, dizziness or lightheadedness, fatigue or lack of energy. If pregnant or breast feeding, ask a health provider before use.

KEEP OUT OF REACH OF CHILDREN

Keep out of reach of of children. If swallowed, get medical help or contact Poison Control Center immediately.

Directions

When practical, clean area with mild soap and warm water and rinse thoroughly. Gently dry by patting or blotting with toilet tissue or soft cloth before applying. Adults and children 12 years and older: apply externally to the affected area up to 6 times a day. Children under 12 years of age: consult a doctor. To use finger cots: Roll one finger cot over finger. Gently squeeze cream onto finger cot. Smooth a layer of the cream over affected area.

Other Information

Store at 25°C (77°F); excursions permitted to 15-30°C (59-86°F) [see USP Controlled Room Temperature].

Inactive Ingredients

acrylamide, allantoin, aloe vera extract, benzyl alcohol, C12-15 alkyl benzoate, carbomer, isohexadecane, polysorbate 80, propylene glycol, purified water, sodium acryloyldimethyl taurate, sodium laureth sulfate, soy lecithin and tocopheryl acetate.

Distributed By: Stratus Pharmaceuticals, Inc.,Miami, FL 33186

PRINCIPAL DISPLAY PANEL - 14.17 g Tube Box

STRATUS
PHARMACEUTICALS INC

NDC 58980-823-05

Net WT. 0.5 oz. / 14.17 g

LIDOCAINE CREAM
5%

ANORECTAL CREAM